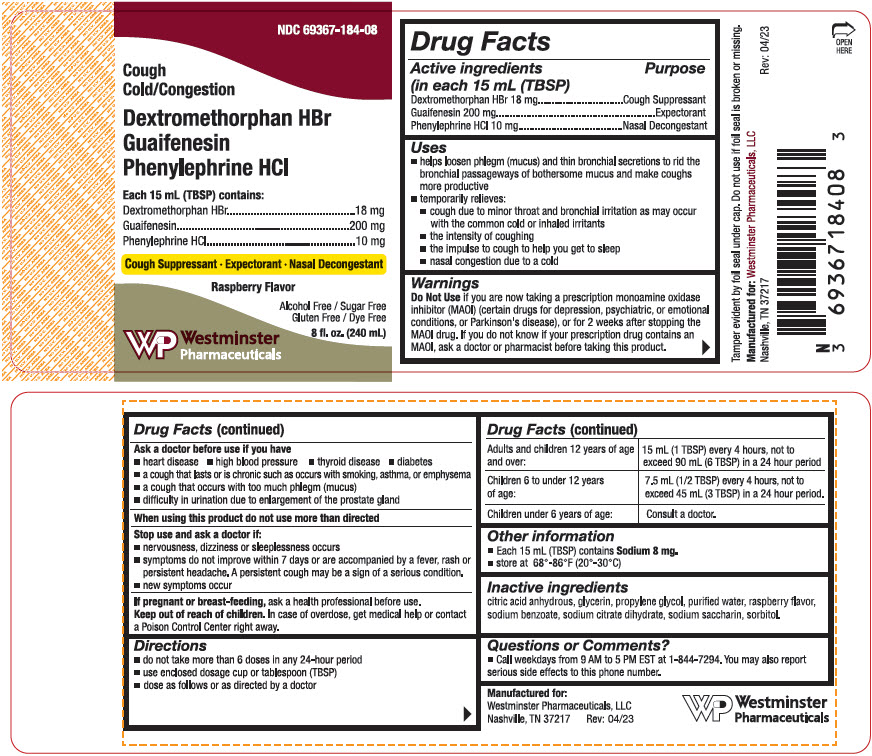 DRUG LABEL: DEXTROMETHORPHAN HYDROBROMIDE, Guaifenesin, and PHENYLEPHRINE HYDROCHLORIDE
NDC: 69367-184 | Form: LIQUID
Manufacturer: Westminster Pharmaceuticals, LLC
Category: otc | Type: HUMAN OTC DRUG LABEL
Date: 20180314

ACTIVE INGREDIENTS: DEXTROMETHORPHAN HYDROBROMIDE 18 mg/15 mL; GUAIFENESIN 200 mg/15 mL; PHENYLEPHRINE HYDROCHLORIDE 10 mg/15 mL
INACTIVE INGREDIENTS: ANHYDROUS CITRIC ACID; GLYCERIN; PROPYLENE GLYCOL; WATER; SORBITOL; SACCHARIN SODIUM; SODIUM BENZOATE; TRISODIUM CITRATE DIHYDRATE

DEXTROMETHORPHAN HYDROBROMIDE, GUAIFENESIN, AND PHENYLEPHRINE HYDROCHLORIDE

Drug Facts

ACTIVE INGREDIENT

Active ingredients (in each 15 mL (TBSP) | Purpose
Dextromethorphan HBr 18 mg | Cough Suppressant
Guaifenesin 200 mg | Expectorant
Phenylephrine HCl 10 mg | Nasal Decongestant

Uses

- helps loosen phlegm (mucus) and thin bronchial secretions to rid the bronchial passageways of bothersome mucus and make coughs more productive
- temporarily relieves:
  - cough due to minor throat and bronchial irritation as may occur with the common cold or inhaled irritants
  - the intensity of coughing
  - the impulse to cough to help you get to sleep
  - nasal congestion due to a cold

Warnings

Do Not Use if you are now taking a prescription monoamine oxidase inhibitor (MAOI) (certain drugs for depression, psychiatric, or emotional conditions, or Parkinson's disease), or for 2 weeks after stopping the MAOI drug. If you do not know if your prescription drug contains an MAOI, ask a doctor or pharmacist before taking this product.

Ask a doctor before use if you have

- heart disease
- high blood pressure
- thyroid disease
- diabetes
- a cough that lasts or is chronic such as occurs with smoking, asthma, or emphysema
- a cough that occurs with too much phlegm (mucus)
- difficulty in urination due to enlargement of the prostate gland

When using this product do not use more than directed

Stop use and ask a doctor if

- nervousness, dizziness or sleeplessness occurs
- symptoms do not improve within 7 days or are accompanied by a fever, rash or persistent headache. A persistent cough may be a sign of a serious condition.
- new symptoms occur

PREGNANCY OR BREAST FEEDING

If pregnant or breast-feeding, ask a health professional before use.

Keep out of reach of children. In case of overdose, get medical help or contact a Poison Control Center right away.

Directions

- do not take more than 6 doses in any 24-hour period
- use enclosed dosage cup or tablespoon (TBSP)
- dose as follows or as directed by a doctor

Adults and children 12 years of age and over: | 15 mL (1 TBSP) every 4 hours, not to exceed 90 mL (6 TBSP) in a 24 hour period
Children 6 to under 12 years of age: | 7.5 mL (1/2 TBSP) every 4 hours, not to exceed 45 mL (3 TBSP) in a 24 hour period.
Children under 6 years of age: | Consult a doctor.

Other information

- Each 15 mL (TBSP) contains Sodium 8 mg.
- store at 68°-86°F (20°-30°C)

Inactive ingredients

citric acid anhydrous, glycerin, propylene glycol, purified water, raspberry flavor, sodium benzoate, sodium citrate dihydrate, sodium saccharin, sorbitol.

Questions or Comments?

- Call weekdays from 9 AM to 5 PM EST at 1-844-7294. You may also report serious side effects to this phone number.

PRINCIPAL DISPLAY PANEL - 240 mL Bottle Label

NDC 69367-184-08

Cough
Cold/Congestion

Dextromethorphan HBr
Guaifenesin
Phenylephrine HCl

Each 15 mL (TBSP) contains:
Dextromethorphan HBr
18 mg
Guaifenesin
200 mg
Phenylephrine HCl
10 mg

Cough Suppressant ∙ Expectorant ∙ Nasal Decongestant

Raspberry Flavor

Alcohol Free / Sugar Free
Gluten Free / Dye Free

8 fl. oz. (240 mL)

Westminster
Pharmaceuticals